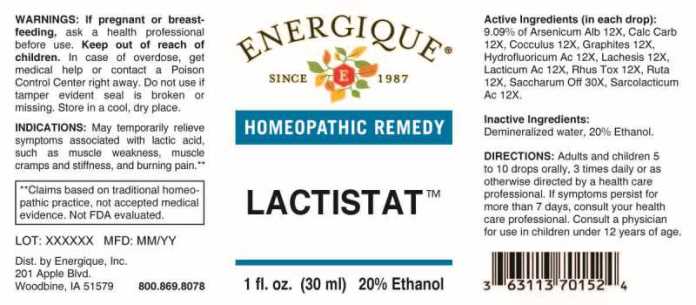 DRUG LABEL: Lactistat
NDC: 44911-0336 | Form: LIQUID
Manufacturer: Energique, Inc.
Category: homeopathic | Type: HUMAN OTC DRUG LABEL
Date: 20241028

ACTIVE INGREDIENTS: ARSENIC TRIOXIDE 12 [hp_X]/1 mL; OYSTER SHELL CALCIUM CARBONATE, CRUDE 12 [hp_X]/1 mL; ANAMIRTA COCCULUS SEED 12 [hp_X]/1 mL; GRAPHITE 12 [hp_X]/1 mL; HYDROFLUORIC ACID 12 [hp_X]/1 mL; LACHESIS MUTA VENOM 12 [hp_X]/1 mL; LACTIC ACID, DL- 12 [hp_X]/1 mL; TOXICODENDRON PUBESCENS LEAF 12 [hp_X]/1 mL; RUTA GRAVEOLENS FLOWERING TOP 12 [hp_X]/1 mL; LACTIC ACID, L- 12 [hp_X]/1 mL; SUCROSE 30 [hp_X]/1 mL
INACTIVE INGREDIENTS: WATER; ALCOHOL

DRUG FACTS:

ACTIVE INGREDIENTS:

(in each drop): 9.09% Arsenicum Album 12X, Calcarea Carbonica 12X, Cocculus Indicus 12X, Graphites 12X, Hydrofluoricum Acidum 12X, Lachesis Mutus 12X, Lacticum Acidum 12X, Rhus Tox 12X, Ruta Graveolens 12X, Sarcolacticum Acidum 12X, Saccharum Officinale 30X.

INDICATIONS:

May temporarily relieve symptoms associated with lactic acid such as muscle weakness, muscle cramps and stiffness, and burning pain.**

**These statements are based upon traditional homeopathic practice. They have not been reviewed by the Food and Drug Administration.

WARNINGS:

If pregnant or breastfeeding, ask a health professional before use.

Keep out of reach of children. In case of overdose, get medical help or contact a Poison Control Center right away.

Do not use if tamper evident seal is broken or missing.

Store in a cool, dry place.

Keep out of reach of children. In case of overdose, get medical help or contact a Poison Control Center right away.

DIRECTIONS:

Adults and children 5 to 10 drops orally, 3 times daily or as otherwise directed by a health care professional. If symptoms persist for more than 7 days, consult your health care professional. Consult a physician for use in children under 12 years of age.

INDICATIONS:

May temporarily relieve symptoms associated with lactic acid such as muscle weakness, muscle cramps and stiffness, and burning pain.**

**These statements are based upon traditional homeopathic practice. They have not been reviewed by the Food and Drug Administration.

INACTIVE INGREDIENTS:

Demineralized water, 20% Ethanol.

QUESTIONS:

Dist. by Energique, Inc.
201 Apple Blvd.
Woodbine, IA 51579 800.868.8078

PACKAGE LABEL DISPLAY:

ENERGIQUE

SINCE 1987

HOMEOPATHIC REMEDY

LACTISTAT

1 fl. oz. (30 ml)